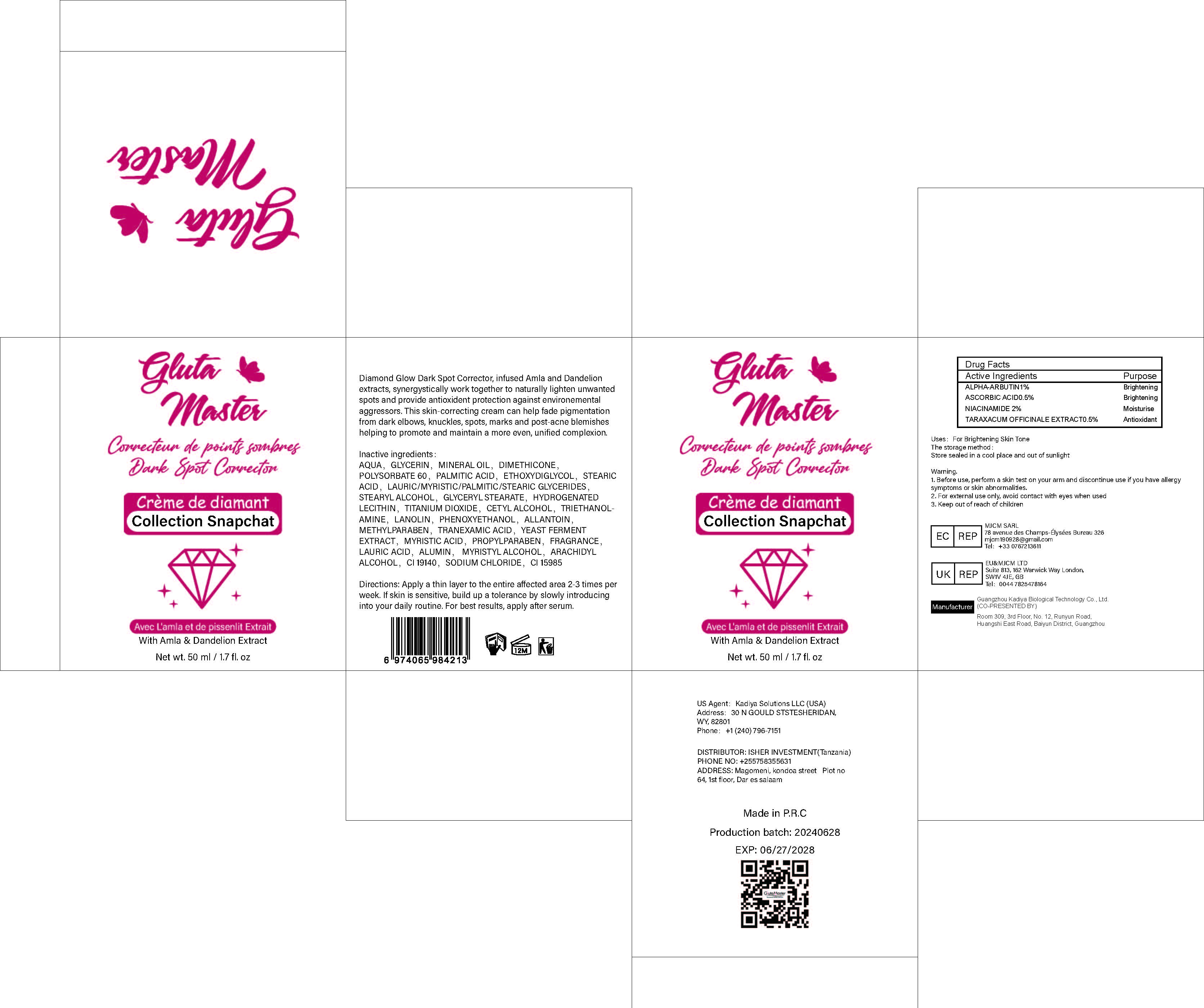 DRUG LABEL: Diamond Glow Dark Spot Corrector Face Cream
NDC: 84423-048 | Form: CREAM, AUGMENTED
Manufacturer: Guangzhou Kadiya Biotechnology Co., Ltd.
Category: otc | Type: HUMAN OTC DRUG LABEL
Date: 20240928

ACTIVE INGREDIENTS: NIACINAMIDE 1 g/50 mL; ALPHA-ARBUTIN 0.5 g/50 mL; ASCORBIC ACID 0.25 g/50 mL; TARAXACUM OFFICINALE ROOT 0.25 g/50 mL
INACTIVE INGREDIENTS: STEARYL ALCOHOL; GLYCERYL MONOSTEARATE; WATER; GLYCERIN; PHENOXYETHANOL; LAURIC ACID; ALUMINUM OXIDE; PALMITIC ACID; METHOXYDIGLYCOL; TITANIUM DIOXIDE; ALLANTOIN; PROPYLPARABEN; MYRISTYL ALCOHOL; FD&C YELLOW NO. 5; SODIUM CHLORIDE; ARACHIDYL ALCOHOL; MINERAL OIL; STEARIC ACID; POLYSORBATE 60; TROLAMINE; METHYLPARABEN; MYRISTIC ACID; FD&C YELLOW NO. 6; TRANEXAMIC ACID; DIMETHICONE; CETYL ALCOHOL; LANOLIN

Uses：
For brightening the face and moisturising the skin.

INACTIVE INGREDIENT

AQUA，GLYCERIN，MINERAL OIL，DIMETHICONE，POLYSORBATE 60，PALMITIC ACID，ETHOXYDIGLYCOL，STEARIC ACID，LAURIC/MYRISTIC/PALMITIC/STEARIC GLYCERIDES，STEARYL ALCOHOL，GLYCERYL STEARATE，HYDROGENATED LECITHIN，TITANIUM DIOXIDE，CETYL ALCOHOL，TRIETHANOLAMINE，LANOLIN，PHENOXYETHANOL，ALLANTOIN，METHYLPARABEN，TRANEXAMIC ACID，YEAST FERMENT EXTRACT，MYRISTIC ACID，PROPYLPARABEN，FRAGRANCE，LAURIC ACID，ALUMIN， MYRISTYL ALCOHOL，ARACHIDYL ALCOHOL，CI 19140，SODIUM CHLORIDE，CI 15985

Warning.
1、For external use only, avoid contact with eyes when used
2、Keep out of reach of children

INDICATIONS AND USAGE

Diamond Glow Dark Spot Corrector, infused Amla and Dandelion extracts, synergystically work together to naturally lighten unwanted spots and provide antioxident protection against environemental aggressors. This skin-correcting cream can help fade pigmentation from dark elbows, knuckles, spots, marks and post-acne blemishes helping to promote and maintain a more even, unified complexion.

DOSAGE AND ADMINISTRATION

Directions: Apply a thin layer to the entire affected area 2-3 times per week. If skin is sensitive, build up a tolerance by slowly introducing into your daily routine. For best results, apply after serum.

KEEP OUT OF REACH OF CHILDREN SECTION

Active Ingredients
ALPHA-ARBUTIN1%
ASCORBIC ACID0.5%
NIACINAMIDE 2%
TARAXACUM OFFICINALE EXTRACT0.5%

PACKAGE LABEL

Active Ingredients
ALPHA-ARBUTIN1%
ASCORBIC ACID0.5%
NIACINAMIDE 2%
TARAXACUM OFFICINALE EXTRACT0.5%
Uses：
For brightening the face and moisturising the skin.
The storage method：
Store sealed in a cool place and out of sunlight
Warning.
1、For external use only, avoid contact with eyes when used
2、Keep out of reach of children
Inactive ingredients：
AQUA，GLYCERIN，MINERAL OIL，DIMETHICONE，POLYSORBATE 60，PALMITIC ACID，ETHOXYDIGLYCOL，STEARIC ACID，LAURIC/MYRISTIC/PALMITIC/STEARIC GLYCERIDES，STEARYL ALCOHOL，GLYCERYL STEARATE，HYDROGENATED LECITHIN，TITANIUM DIOXIDE，CETYL ALCOHOL，TRIETHANOLAMINE，LANOLIN，PHENOXYETHANOL，ALLANTOIN，METHYLPARABEN，TRANEXAMIC ACID，YEAST FERMENT EXTRACT，MYRISTIC ACID，PROPYLPARABEN，FRAGRANCE，LAURIC ACID，ALUMIN， MYRISTYL ALCOHOL，ARACHIDYL ALCOHOL，CI 19140，SODIUM CHLORIDE，CI 15985